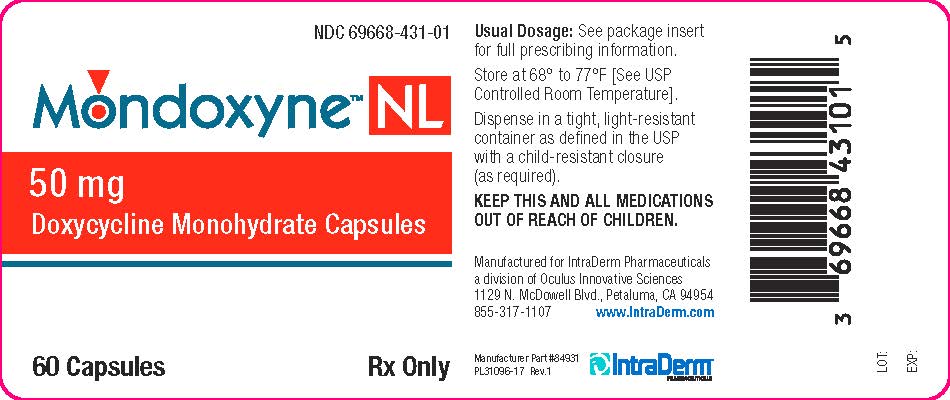 DRUG LABEL: Mondoxyne
NDC: 69668-431 | Form: CAPSULE
Manufacturer: Oculus Innovative Sciences
Category: prescription | Type: HUMAN PRESCRIPTION DRUG LABEL
Date: 20150902

ACTIVE INGREDIENTS: DOXYCYCLINE 50 mg/50 mg

Mondoxyne NL 50mg

Mondoxyne NL 50mg Label Warning

Keep this and all medications out of the reach of children.